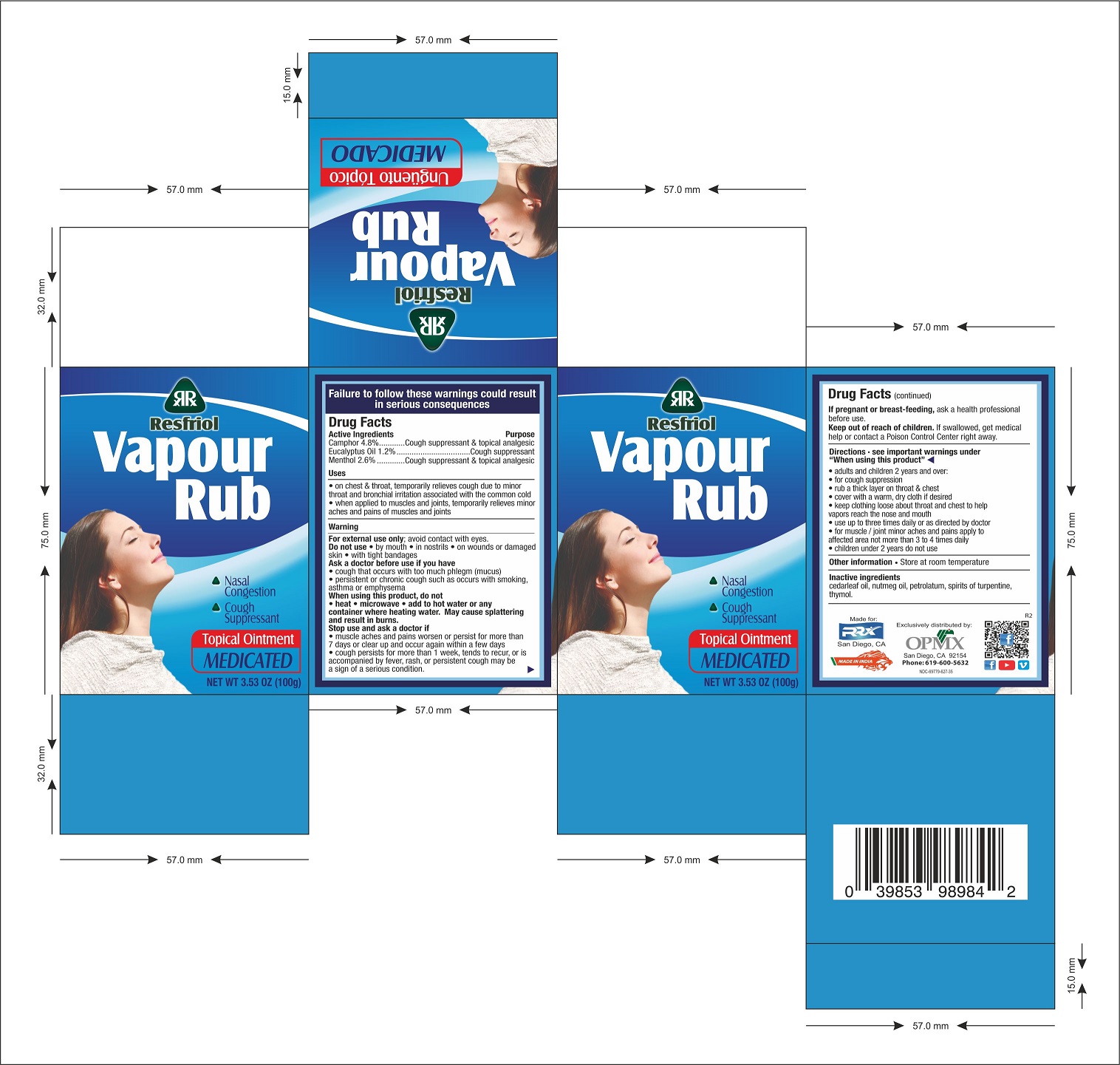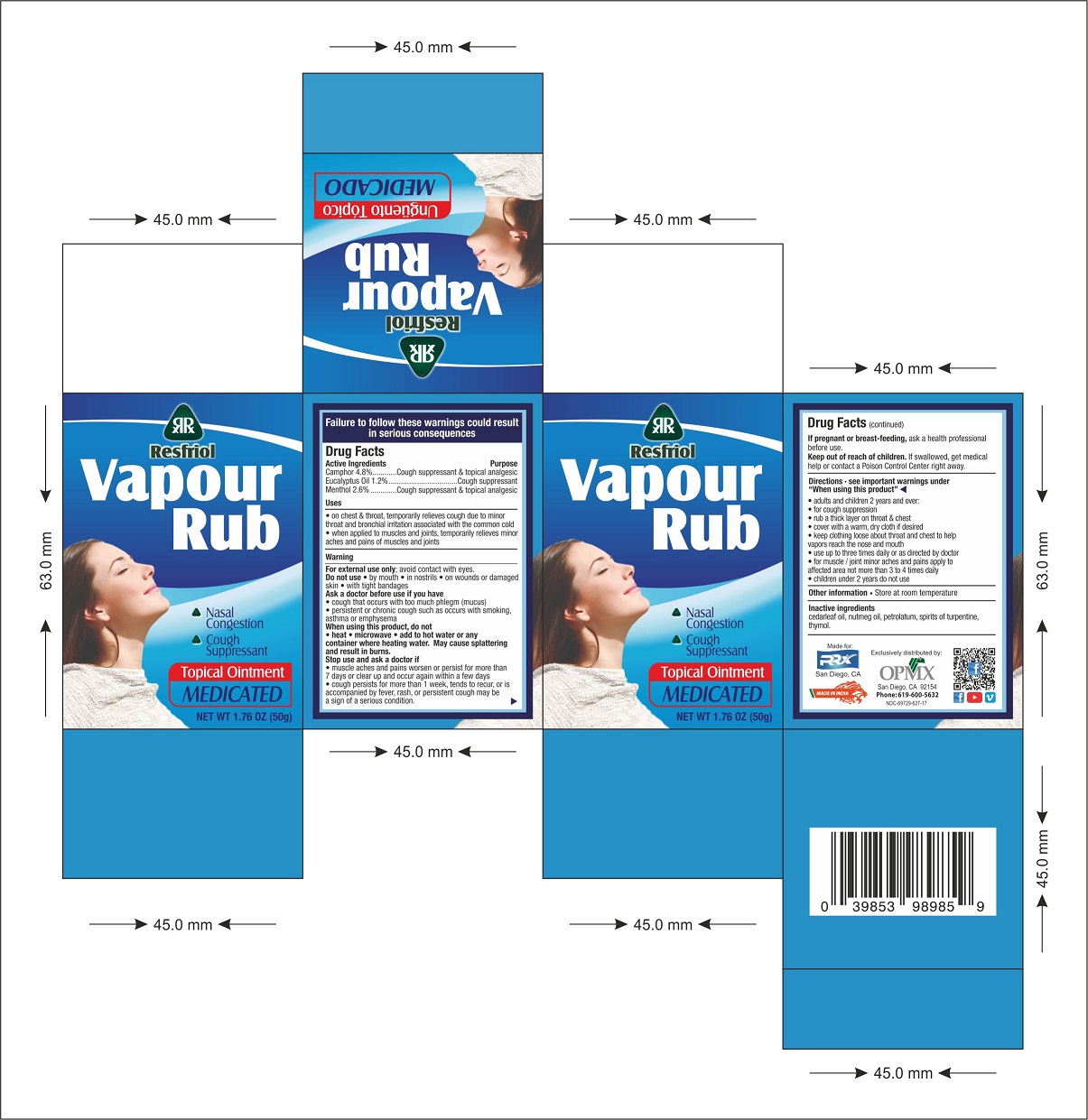 DRUG LABEL: VAPOUR RUB
NDC: 69729-101 | Form: OINTMENT
Manufacturer: OPMX LLC
Category: otc | Type: HUMAN OTC DRUG LABEL
Date: 20180716

ACTIVE INGREDIENTS: CAMPHOR (SYNTHETIC) 4.8 g/100 g; EUCALYPTUS OIL 1.2 g/100 g; MENTHOL 2.6 g/100 g
INACTIVE INGREDIENTS: CEDAR LEAF OIL; NUTMEG OIL; PETROLATUM; TURPENTINE OIL; THYMOL

VAPOUR RUB

Active Ingredients

CAMPHOR 4.8%

EUCALYPTUS 1.2%

MENTHOL 2.6%

Purpose

COUPH SUPPRESSANT & TOPICAL ANALGESIC

COUGH SUPPRESSANT

COUPH SUPPRESSANT & TOPICAL ANALGESIC

Uses

- ON CHEST & THROAT, TEMPORARILY RELIEVES COUGH DUE TO MINOR THROAT AND BRONCHIAL IRRITATION ASSOCIATED WITH THE COMMON COLD
- WHEN APPLIED TO MUSCLES AND JOINTS, TEMPORARILY RELIEVES MINOR ACHES AND PAINS OF MUSCLES AND JOINTS

Warnings

FOR EXTERNAL USE ONLY; AVOID CONTACT WITH EYES.

DO NOT USE

- BY MOUTH
- IN NOSTRILS
- ON WOUNDS OR DAMAGED SKIN
- WITH TIGHT BANDAGES

ASK A DOCTOR BEFORE USE IF YOU HAVE

- COUGH THAT OCCURS WITH TOO MUCH PHLEGM (MUCUS)
- PERSISTANT OR CHRONIC COUGH SUCH AS OCCURS WITH SMOKING, ASTHMA OR EMPHYSEMA

WHEN USING THIS PRODUCT, DO OT

- HEAT
- MICROWAVE
- ADD TO HOT WATER OR ANY CONTAINER WHERE HEATING WATER. MAY CAUSE SPLATTERING AND RESULT IN BURNS.

STOP USE AND ASK A DOCTOR IF

- MUSCLE ACHES AND PAINS WORSEN OR PERSIST FOR MORE THAN 7 DAYS OR CLEAR UP AND OCCUR AGAIN WITHIN A FEW DAYS
- COUGH PERSISTS FOR MORE THAN 1 WEEK, TENDS TO RECUR, OR IS ACCOMPANIED BY FEVER, RASH, OR PERSISTENT COUGH MAY BE A SIGN OF A SERIOUS CONDITION.

IF PREGNANT OR BRAST-FEEDING, ASK A HEALTH PROFESSIONAL BEFORE USE.

Keep out of reach of children.

If swallowed, get medical help or contact a Poison Control Center right away.

DIRECTIONS - SEE IMPORTANT WARNINGS UNDER "WHEN USING THIS PRODUCT"

- ADULTS AND CHILDREN 2 YEARS AND OVER:
- FOR COUGH SUPPRESSION
- RUB A THICK LAYER ON THROAT & CHEST
- COVER WITH A WARM, DRY CLOTH IF DESIRED
- KEEP CLOTHING LOOSE ABOUT THROAT AND CHEST TO HELP VAPORS REACH THE NOSE AND MOUTH
- USE UP TO THREE TIMES DAILY OR AS DIRECTED BY A DOCTOR
- FOR MUSCLE/JOINT MINOR ACHES AND PAINS APPLY TO AFFECTED AREA NOT MORE THAN 3 TO 4 TIMES DAILY
- CHILDREN UNDER 2 YEARS DO NOT USE

Other information

- STORE AT ROOM TEMPERATURE

Inactive ingredients

CEDARLEAF OIL, NUTMEG OIL, PETROLATUM, SPIRITS OF TURPENTINE, THYMOL